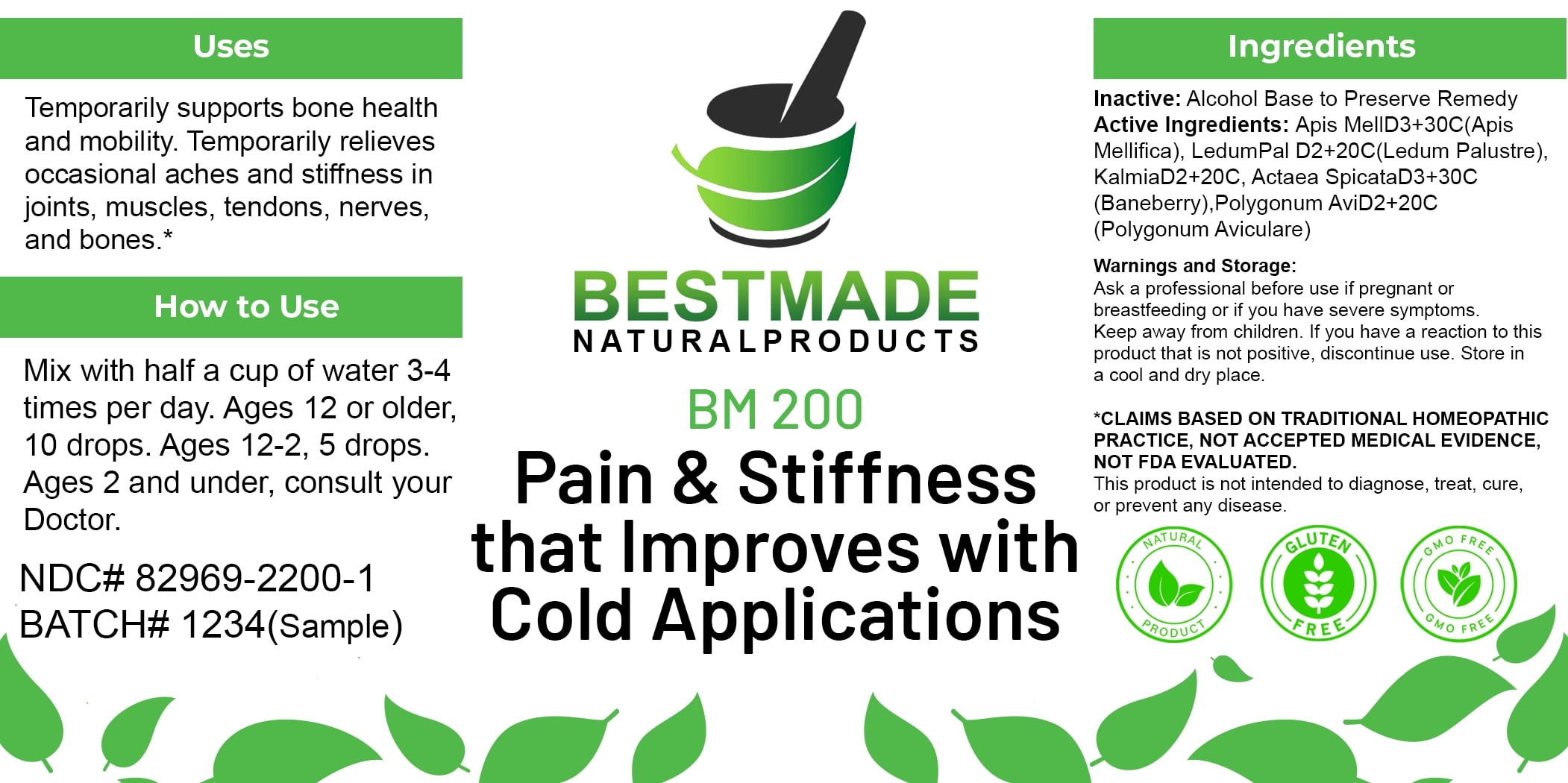 DRUG LABEL: Bestmade Natural Products BM200
NDC: 82969-2200 | Form: LIQUID
Manufacturer: Bestmade Natural Products
Category: homeopathic | Type: HUMAN OTC DRUG LABEL
Date: 20250225

ACTIVE INGREDIENTS: APIS MELLIFERA 30 [hp_C]/30 [hp_C]; KALMIA LATIFOLIA LEAF 30 [hp_C]/30 [hp_C]; POLYGONUM AVICULARE WHOLE 30 [hp_C]/30 [hp_C]; LEDUM PALUSTRE TWIG 30 [hp_C]/30 [hp_C]; ACTAEA SPICATA ROOT 30 [hp_C]/30 [hp_C]
INACTIVE INGREDIENTS: ALCOHOL 30 [hp_C]/30 [hp_C]

BM200

DOSAGE AND ADMINISTRATION

How to Use

Mix with half a cup of water 3-4 times per day. Ages 12 or older, 10 drops. Ages 12-2, 5 drops. Ages 2 and under, consult your Doctor.

Uses

Temporarily supports bone health and mobility. Temporarily relieves occasional aches and stiffness in joints, muscles, tendons, nerves, and bones.*

*CLAIMS BASED ON TRADITIONAL HOMEOPATHIC PRACTICE, NOT ACCEPTED MEDICAL EVIDENCE. NOT FDA EVALUATED.

This product is not intended to diagnose, treat, cure, or prevent any disease.

INACTIVE INGREDIENT

Ingredients

Inactive: Alcohol Base to Preserve Remedy

ACTIVE INGREDIENT

Active Ingredients: Apis MellD3+30C(Apis Mellifica), Ledum Pal D2+20C(Ledum Palustre), KalmiaD2+20C, Actaea SpicataD3+30C(Baneberry), Polygonum AviD2+20C(Polygonum Aviculare)

KEEP OUT OF REACH OF CHILDREN

Warnings and Storage:

Ask a professional before use if pregnant or breastfeeding or if you have severe symptoms. Keep away from children. If you have a reaction to this product that is not positive, discontinue use. Store in a cool and dry place.

Warnings and Storage:

Ask a professional before use if pregnant or breastfeeding or if you have severe symptoms. Keep away from children. If you have a reaction to this product that is not positive, discontinue use. Store in a cool and dry place.

*CLAIMS BASED ON TRADITIONAL HOMEOPATHIC PRACTICE, NOT ACCEPTED MEDICAL EVIDENCE. NOT FDA EVALUATED.

This product is not intended to diagnose, treat, cure, or prevent any disease.

Uses

Temporarily supports bone health and mobility. Temporarily relieves occasional aches and stiffness in joints, muscles, tendons, nerves, and bones.*

*CLAIMS BASED ON TRADITIONAL HOMEOPATHIC PRACTICE, NOT ACCEPTED MEDICAL EVIDENCE. NOT FDA EVALUATED.

This product is not intended to diagnose, treat, cure, or prevent any disease.

Entire package label